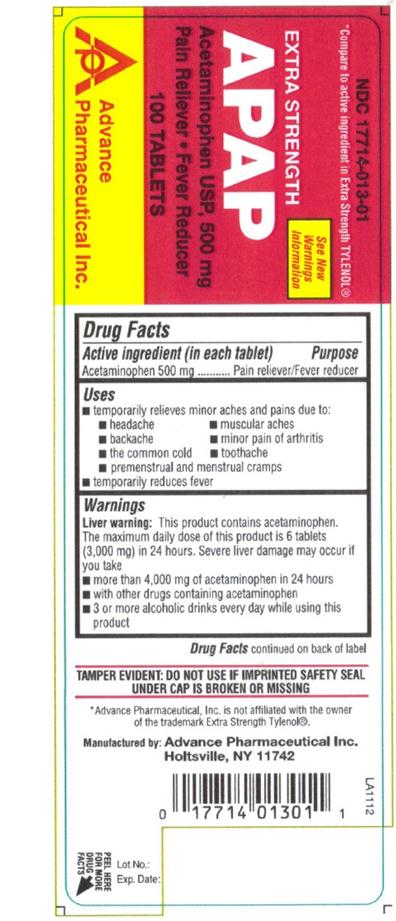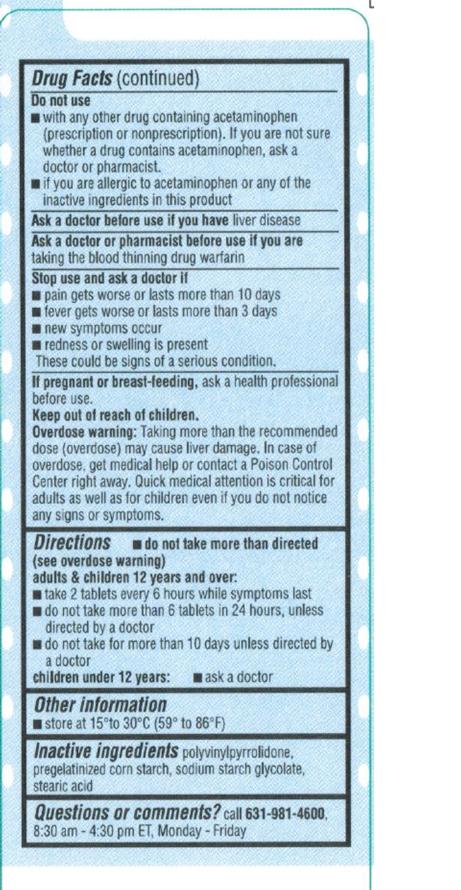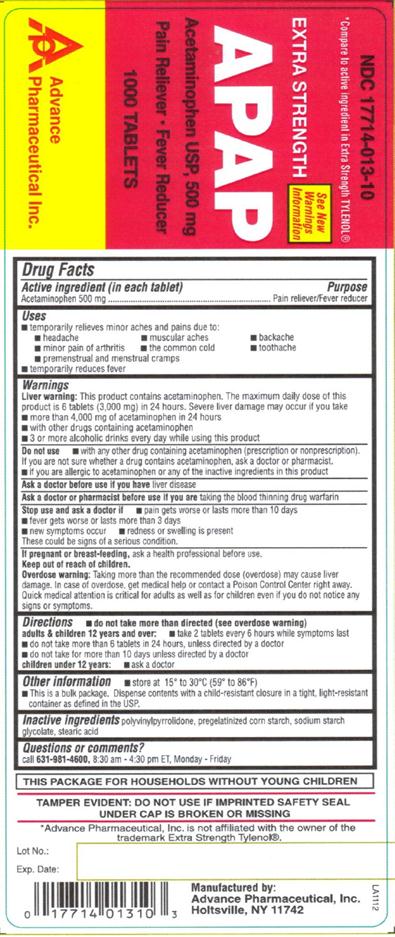 DRUG LABEL: APAP
NDC: 17714-013 | Form: TABLET
Manufacturer: Advance Pharmaceutical Inc.
Category: otc | Type: HUMAN OTC DRUG LABEL
Date: 20171222

ACTIVE INGREDIENTS: ACETAMINOPHEN 500 mg/1 1
INACTIVE INGREDIENTS: POVIDONE; STARCH, CORN; SODIUM STARCH GLYCOLATE TYPE A POTATO; STEARIC ACID

ACETAMINOPHEN USP 500 mg

Active Ingredient

(in each tablet)

Acetaminophen 500 mg

Purpose

Pain Reliever / Fever Reducer

Uses

temporarily relieves minor aches and pains due to

- headache
- muscular aches
- backache
- minor pain of arthritis
- the common cold
- toothache
- premenstrual and menstrual cramps
- temporarily reduces fever

Warnings

Liver warning: this product contains acetaminophen. The maximum daily dose of this product is 6 tablets (3,000 mg) in 24 hours. Severe liver damage may occur if you take

- more than 4,000 mg of acetaminophen in 24 hours
- with other drugs containing acetaminophen
- 3 or more alcoholic drinks every day while using this product

do not use

- with any other drug containing acetaminophen (prescription or non prescription). If you are not sure whether a drug contains acetaminophen, ask a doctor or pharmacist.
- If you are allergic to acetaminophen or any of the inactive ingredients in this product

Ask a doctor before use if the you have liver disease

Ask a doctor or pharmacist before use if you are taking the blood thinning drug warfarin

Stop use and ask a doctor if

- pain gets worse or lasts more than 10 days
- fever gets worse or lasts more than 3 days
- redness or swelling is present
- new symptoms occur

- these could be signs of a serious condition.

If pregnant or breast-feeding, ask a health professional before use.

Keep out of reach of children.

Overdose warning: Taking more than the recommended dose (overdose) may cause liver damage. In case of overdose, get medical help or contact a Poison Control Center right away. Quick medical attention is critical for adults as well as for children even if you do not notice any signs or symptoms.

Directions

- Do not take more than directed (see over dose warning) adults & children 12 years and over :
- take 2 tablets every 6 hours while symptoms last
- do not take more than 6 tablets in 24 hours, unless directed by a doctor
- do not take for more than 10 days unless directed by a doctor
- children under 12 years : ask a doctor

Other Information

- store at 15-30 °C (59-86 °F)

For Bulk package: This is a bulk package, dispense contents with a child-resistant closure in a tight, light resistant container as defined in the USP.

Inactive Ingredients

polyvinylpyrrolidone, pregelatinized corn starch, sodium starch glycolate, stearic acid

Questions or Comments

Call 631-981-4600 8.30 am- 4.30 pm ET, Monday-Friday

TAMPER EVIDENT: DO NOT USE IF IMPRINTED SAFETY SEAL UNDER CAP IS BROKEN OR MISSING

Manufactured by: Advance Pharmaceutical, Inc. Holtsville, NY 11742

PACKAGE LABEL.PRINCIPAL DISPLAY PANEL

NDC: 17714-013-01 – 100 COUNT

NDC: 17714-013-10 – 1000 COUNT